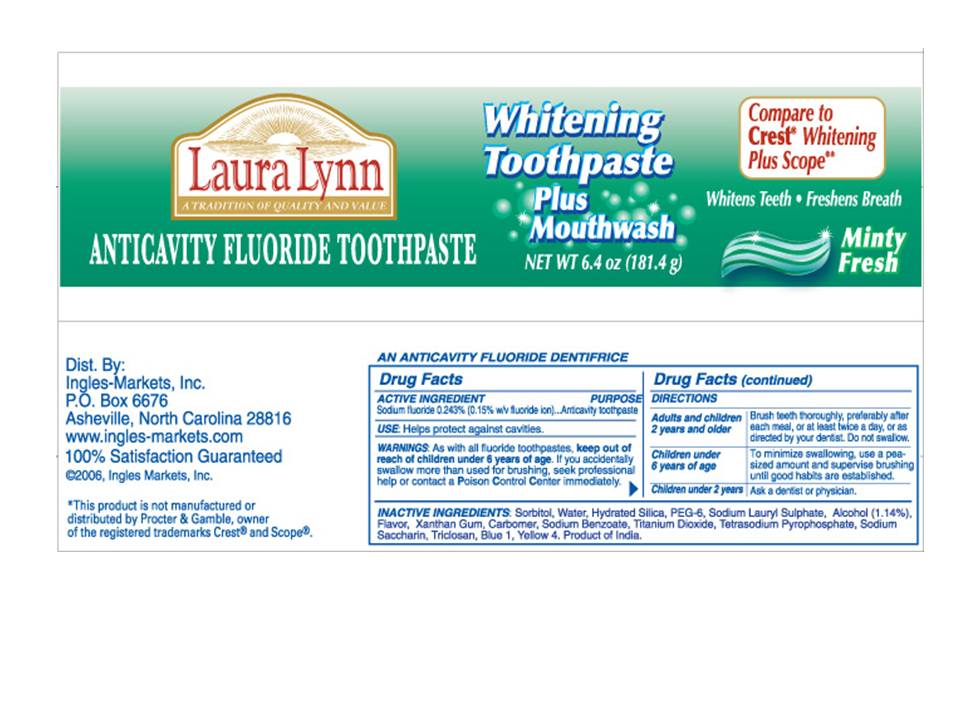 DRUG LABEL: Laura Lynn Anticavity Whitening plus Mouthwash
NDC: 62936-0042 | Form: PASTE
Manufacturer: Ingles Market Inc
Category: otc | Type: HUMAN OTC DRUG LABEL
Date: 20110124

ACTIVE INGREDIENTS: SODIUM FLUORIDE 2.43 mg/1 g
INACTIVE INGREDIENTS: SORBITOL; HYDRATED SILICA; POLYETHYLENE GLYCOL 300; SODIUM LAURYL SULFATE; ALCOHOL 1.14 mg/1 g; XANTHAN GUM; CARBOMER 934; SODIUM BENZOATE; TITANIUM DIOXIDE; SODIUM PYROPHOSPHATE; SACCHARIN SODIUM; FD&C BLUE NO. 1; FERRIC OXIDE YELLOW; WATER

Laura Lynn Anticavity Fluoride Whitening Toothpaste Plus Mouthwash

ACTIVE INGREDIENT

Sodium Fluoride 0.243% (0.15% with fluoride ion)....Anticavity toothpaste

USE

Helps protect against cavities.

WARNINGS

As with all fluoride toothpastes, keep out of reach of
children under 6 years of age. If you accidentally
swallow more than used for brushing, seek professional
help or contact Poison Control Center immediately.

Directions

Adults and children Brush teeth thoroughly, preferably after
2 years and older each meal, or at least twice a day, or as
directed by your dentist. Do not swallow.

Children under To minimize swallowing, use a pea-
6 years of age sized amount and supervise brushing
until good habits are established.

Children under 2 years Ask a dentist or physician.

Inactive Ingredients:

Sorbitol,Water,Hydrated Silica,PEG-6,Sodium Lauryl Sulphate,Alcohol (1.14%),Flavor,Xanthan Gum,Sodium Benzoate,Titanium Dioxide,Tetrasodium Pyrophosphate,Sodium Saccharin,Triosan,Blue 1,Yellow 4